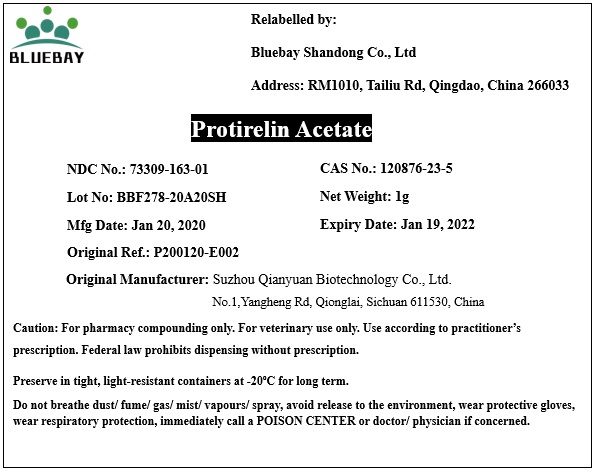 DRUG LABEL: Protirelin Acetate
NDC: 73309-163 | Form: POWDER
Manufacturer: BLUEBAY SHANDONG CO.,LTD
Category: other | Type: BULK INGREDIENT
Date: 20200708

ACTIVE INGREDIENTS: protirelin 1 g/1 g

Protirelin Acetate